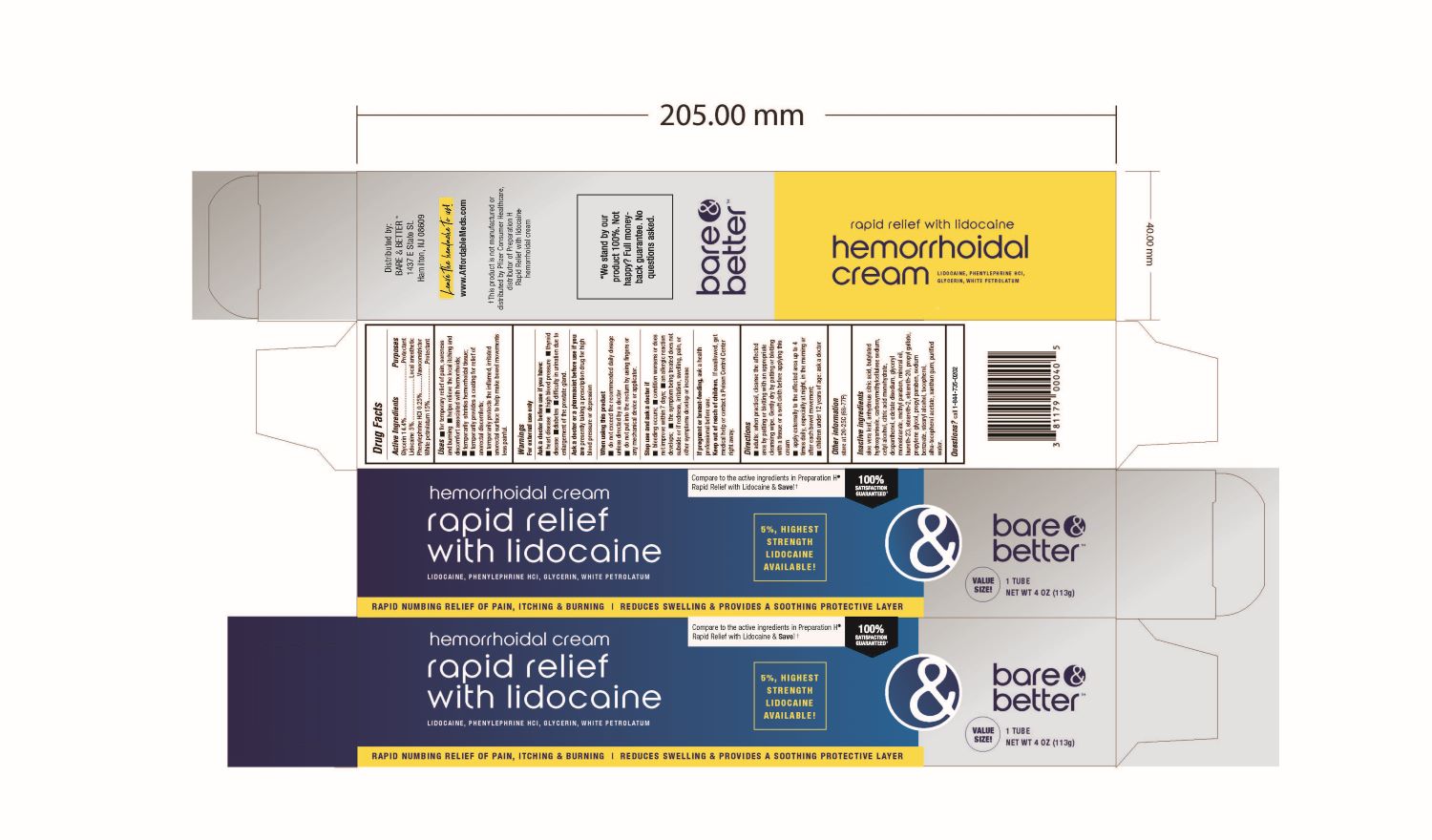 DRUG LABEL: Glycerin, Lidocaine, Petrolatum, and Phenylephrine Hydrochloride
NDC: 55629-051 | Form: CREAM
Manufacturer: ONE2ZEE LIMITED LIABILITY COMPANY
Category: otc | Type: HUMAN OTC DRUG LABEL
Date: 20210208

ACTIVE INGREDIENTS: GLYCERIN 144 mg/1 g; LIDOCAINE 50 mg/1 g; PETROLATUM 150 mg/1 g; PHENYLEPHRINE HYDROCHLORIDE 2.5 mg/1 g
INACTIVE INGREDIENTS: ALOE VERA LEAF; ANHYDROUS CITRIC ACID; BUTYLATED HYDROXYANISOLE; CARBOXYMETHYLCELLULOSE SODIUM; CETYL ALCOHOL; CITRIC ACID MONOHYDRATE; EDETATE DISODIUM; DEXPANTHENOL; GLYCERYL MONOSTEARATE; MINERAL OIL; LAURETH-23; STEARETH-2; STEARETH-20; PROPYL GALLATE; PROPYLENE GLYCOL; PROPYLPARABEN; SODIUM BENZOATE; STEARYL ALCOHOL; TOCOPHEROL; .ALPHA.-TOCOPHEROL ACETATE; XANTHAN GUM; WATER

Glycerin, Lidocaine, Petrolatum, and Phenylephrine Hydrochloride

Active Ingredient:

Glycerin 14.4%
Lidocaine 5%
Phenylephrine HCl 0.25%
White petrolatum 15%

Purpose

- Protectant
- Local anesthetic
- Vasoconstrictor
- Protectant

Uses:

- For temporary relief of pain, soreness and burning
- Helps relieve the local itching and discomfort associated with hemorrhoids
- Temporarily shrinks hemorrhoidal tissue
- Temporarily provides a coating for relief of anorectal discomforts
- Temporarily protects the inflamed irritated anorectal surface to help make bowel movements less painful

Warnings:

- Ask a doctor before use if you have
- Ask a doctor or pharmacist before use if you are presently taking a prescription drug for high blood pressure or depression.

Directions:

- Adults: when practical, cleanse the affected area by patting or blotting with an appropriate cleansing wipe. Gently dry by patting or blotting with a tissue or a soft cloth before applying this cream.
- Apply externally to the affected area up to 4 times daily, especially at night, in the morning or after each bowel movement
- Children under 12 years of age: ask a doctor

Keep out of reach of children. If swallowed, get medical help or contact a Poison Control Center right
away.

PREGNANCY OR BREAST FEEDING

If pregnant or breast-feeding, ask a health professional before use.

Inactive Ingredients:

aloe vera leaf, anhydrous citric acid, butylated hydroxyanisole, carboxymethylcellulose sodium, cetyl alcohol, citric acid monohydrate, dexpanthenol, edetate disodium, glyceryl monosterate, methylparaben, mineral oil, laureth-23, steareth-2, steareth-20, propyl gallate, propylene glycol, propylparaben, sodium benzoate, tocopherol, alpha.- tocopherol acetate, xanthan gum, water

Other Information:

Store at 20-25°C (68-77°F) Do not use if tamper evident packaging has been breached or is missing.

Distributed by: Wellspring Airmont, NY 10952 U.S.A.